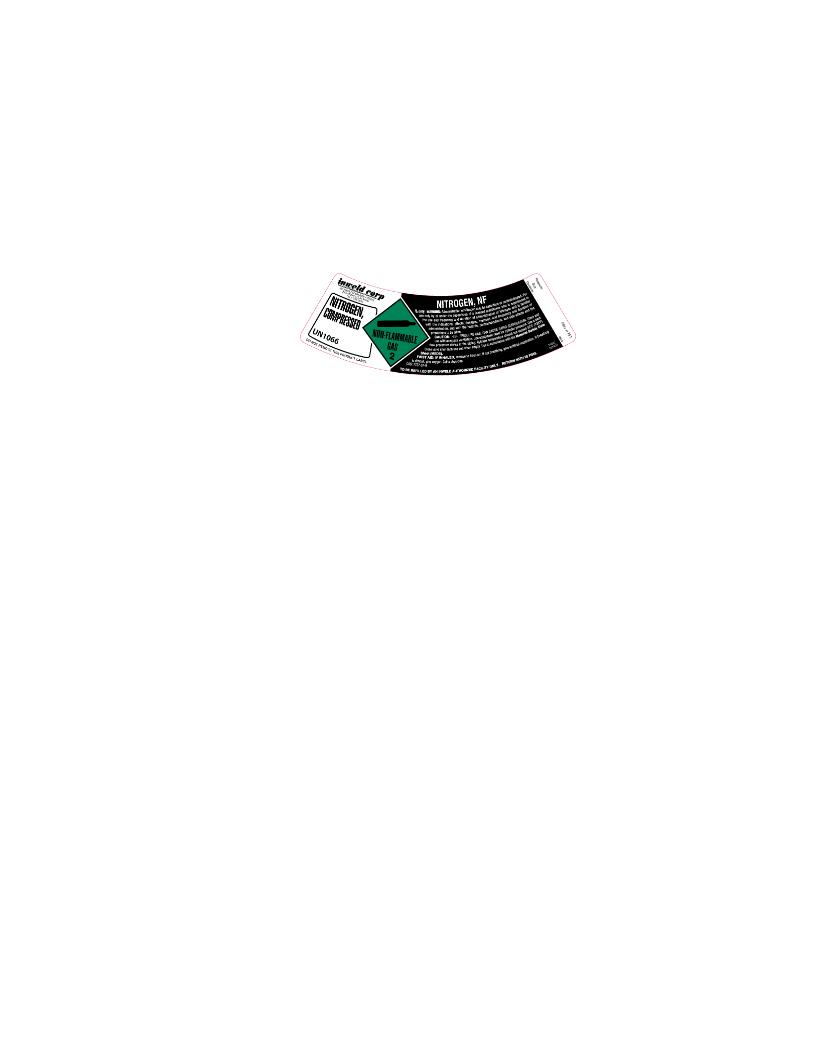 DRUG LABEL: Nitrogen
NDC: 49778-003 | Form: GAS
Manufacturer: American Welding & Gas
Category: prescription | Type: HUMAN PRESCRIPTION DRUG LABEL
Date: 20100412

ACTIVE INGREDIENTS: Nitrogen 99 mL/100 mL

Compressed Nitrogen Label

PACKAGE LABEL

NITROGEN,
COMPRESSED

UN1066

7727-37-9

NITROGEN, NF
Pressure: ___________ PSIG at 70°F
Size: _______________
Contents: ___________ Liters
DO NOT REMOVE THIS PRODUCT LABEL.

Rx Only. WARNING: Administration of Nitrogen may be hazardous or contraindicated. For use only by or under the supervision of a licensed practitioner who is experienced the use and frequency and duration of administration of Nitrogen and is familiar with the indications, effects, dosages, methods, and frequency and duration of administration, and with the hazards, contraindications, and side effects and the precautions to be taken.

CAUTION: HIGH PRESSURE GAS. CAN CAUSE RAPID SUFFOCATION. Store and use with adequate ventilation. Use equipment rated for cylinder pressure. Use a back flow preventive device in the piping. Cylinder temperature should not exceed 52°C (125°F). Close valve after each use and when empty. Use in accordance with the Material Safety Data Sheet (MSDS).

FIRST AID:
IF INHALED, remove to fresh air. If not breathing, give artificial respiration. If breathing is difficult, give oxygen. Call a physician.
TO BE REFILLED BY AN INWELD AUTHORIZED FACILITY ONLY. RETURN WITH 25 PSIG.